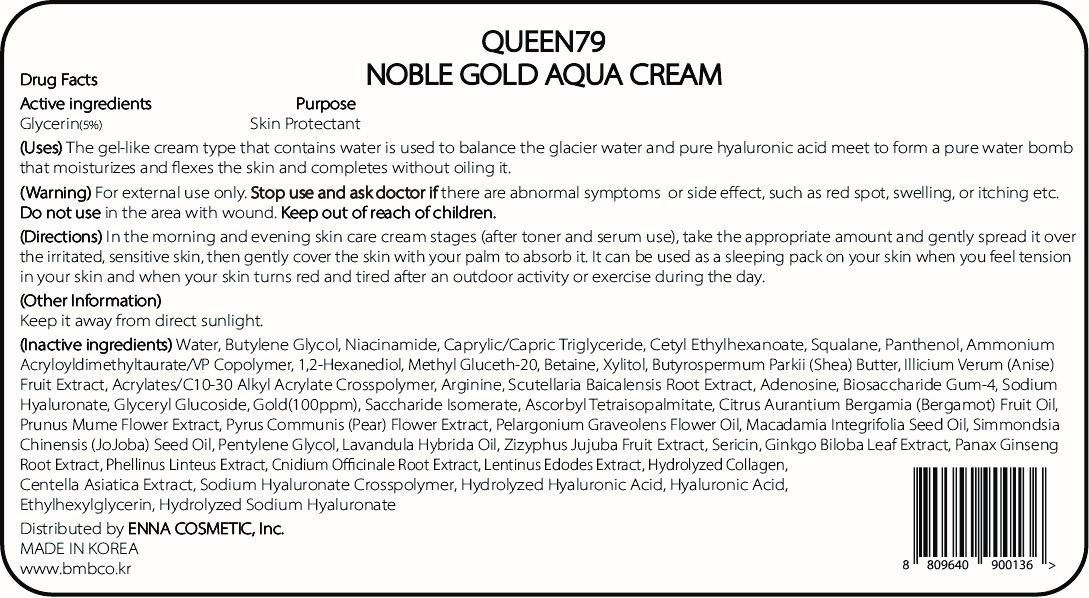 DRUG LABEL: QUEEN79 NOBLE GOLD AQUACREAM
NDC: 81810-304 | Form: CREAM
Manufacturer: ENNA COSMETIC, Inc.
Category: otc | Type: HUMAN OTC DRUG LABEL
Date: 20230531

ACTIVE INGREDIENTS: GLYCERIN 5 mg/100 mL
INACTIVE INGREDIENTS: CNIDIUM OFFICINALE ROOT; WATER; BUTYLENE GLYCOL; SILK SERICIN; PRUNUS MUME FLOWER; ETHYLHEXYLGLYCERIN; BETAINE; GINKGO; PYRUS COMMUNIS FLOWER; HYALURONIC ACID; JOJOBA OIL; MEDIUM-CHAIN TRIGLYCERIDES; 1,2-HEXANEDIOL; HYALURONATE SODIUM; SCUTELLARIA BAICALENSIS ROOT; METHYL GLUCETH-20; SHEA BUTTER; CENTELLA ASIATICA; SACCHARIDE ISOMERATE; LAVANDIN OIL; ASIAN GINSENG; NIACINAMIDE; BIOSACCHARIDE GUM-4; CETYL ETHYLHEXANOATE; SQUALANE; XYLITOL; BERGAMOT OIL; PELARGONIUM GRAVEOLENS FLOWER OIL; PENTYLENE GLYCOL; PANTHENOL; STAR ANISE FRUIT; AMMONIUM ACRYLOYLDIMETHYLTAURATE/VP COPOLYMER; CARBOMER INTERPOLYMER TYPE A (55000 CPS); ARGININE; ADENOSINE; GOLD; ASCORBYL TETRAISOPALMITATE; JUJUBE FRUIT; LENTINULA EDODES MYCELIUM; MACADAMIA OIL

81810-304 QUEEN79 NOBLE GOLD AQUA CREAM

Active ingredients

Glycerin(5%)

Purpose

Skin Protectant

Uses

The gel-like cream type that contains water is used to balance the glacier water and pure hyaluronic acid meet to form a pure water bomb that moisturizes and flexes the skin and completes without oiling it.

Warning

For external use only

Stop use and ask doctor if

there are abnormal symptoms or side effects, such as red spot, swelling, or itching etc.

Do not use

in the area with wound.

Keep out of reach of children

Directions

In the morning and evening skin care cream stages (after toner and serum use), take the appropriate amount and gently spread it over the irritated, sensitive skin, then gently cover the skin with your palm to absorb it. It can be used as a sleeping pack on your skin when you feel tension in your skin and when your skin turns red and tired after an outdoor activity or exercise during the day.

Other Information

Keep it away from direct sunlight.

Inactive ingredients

Water, Butylene Glycol, Niacinamide, Caprylic/Capric Triglyceride, Cetyl Ethylhexanoate, Squalane, Panthenol, Ammonium Acryloyldimethyltaurate/VP Copolymer, 1,2-Hexanediol, Methyl Gluceth-20, Betaine, Xylitol, Butyrospermum Parkii (Shea) Butter, Illicium Verum (Anise) Fruit Extract, Acrylates/C10-30 Alkyl Acrylate Crosspolymer, Arginine, Scutellaria Baicalensis Root Extract, Adenosine, Biosaccharide Gum-4, Sodium Hyaluronate, Glyceryl Glucoside, Gold(100ppm), Saccharide Isomerate, Ascorbyl Tetraisopalmitate, Citrus Aurantium Bergamia (Bergamot) Fruit Oil, Prunus Mume Flower Extract, Pyrus Communis (Pear) Flower Extract, Pelargonium Graveolens Flower Oil, Macadamia Integrifolia Seed Oil, Simmondsia Chinensis (JoJoba) Seed Oil, Pentylene Glycol, Lavandula Hybrida Oil, Zizyphus Jujuba Fruit Extract, Sericin, Ginkgo Biloba Leaf Extract, Panax Ginseng Root Extract, Phellinus Linteus Extract, Cnidium Officinale Root Extract, Lentinus Edodes Extract, Hydrolyzed Collagen, Centella Asiatica Extract, Sodium Hyaluronate Crosspolymer, Hydrolyzed Hyaluronic Acid, Hyaluronic Acid, Ethylhexylglycerin, Hydrolyzed Sodium Hyaluronate